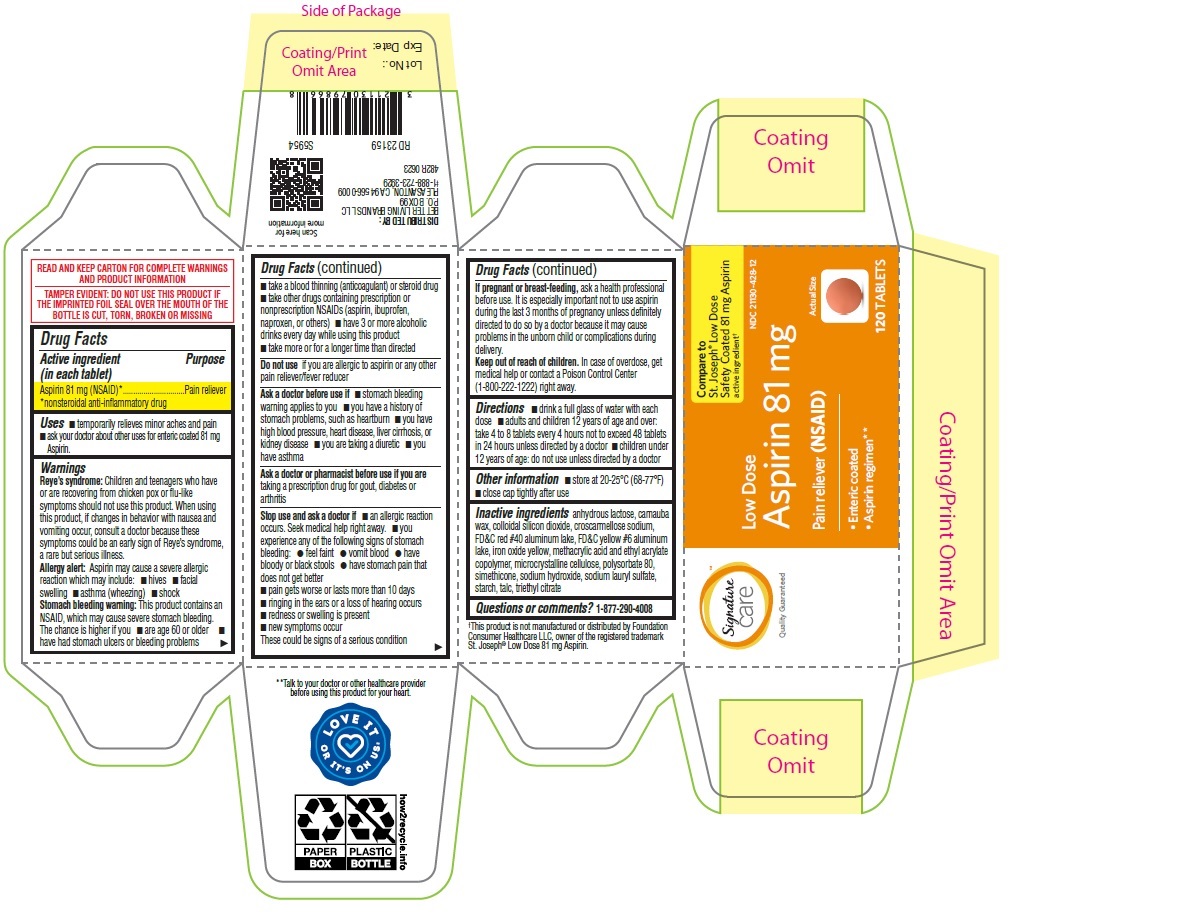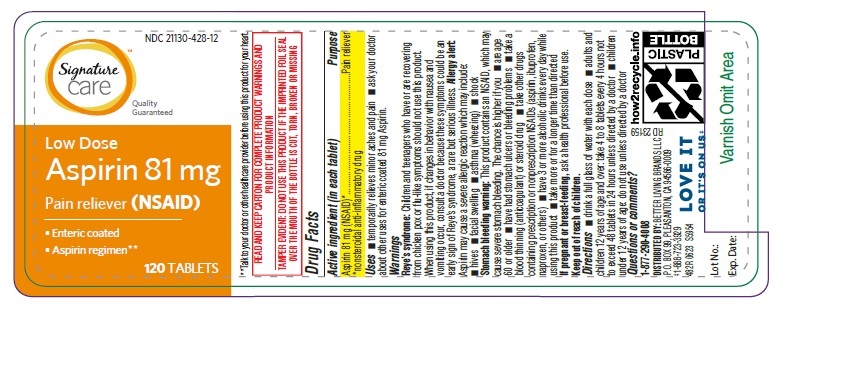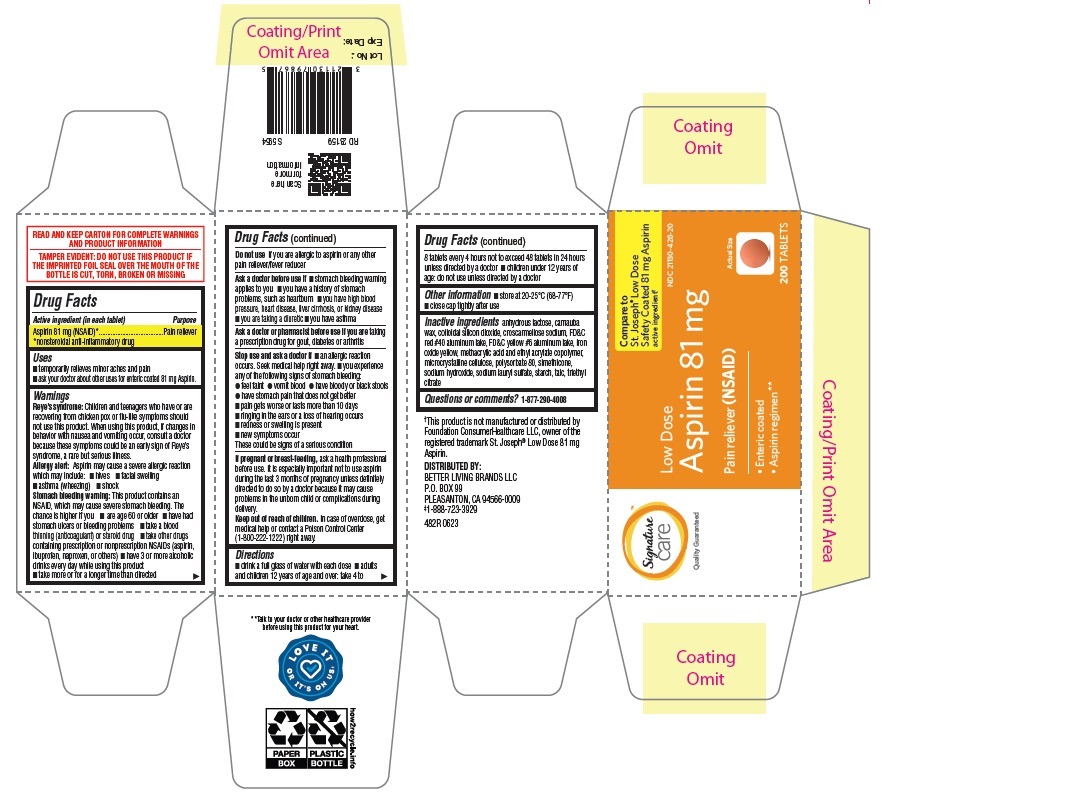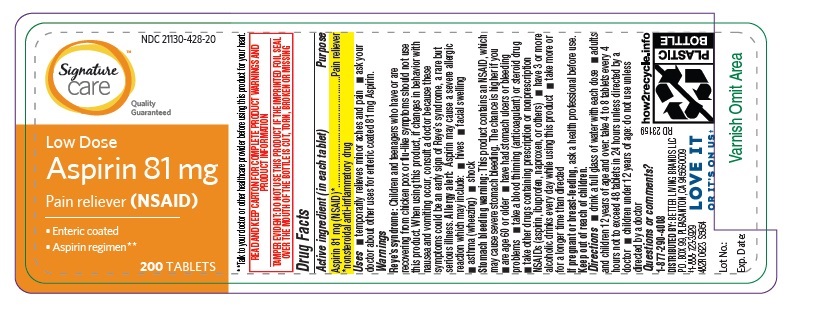 DRUG LABEL: Aspirin 81mg
NDC: 21130-428 | Form: TABLET, DELAYED RELEASE
Manufacturer: BETTER LIVING BRANDS LLC.
Category: otc | Type: HUMAN OTC DRUG LABEL
Date: 20250205

ACTIVE INGREDIENTS: ASPIRIN 81 mg/1 1
INACTIVE INGREDIENTS: STARCH, CORN; ANHYDROUS LACTOSE; CARNAUBA WAX; FD&C RED NO. 40 ALUMINUM LAKE; SODIUM HYDROXIDE; SILICON DIOXIDE; CROSCARMELLOSE SODIUM; POLYSORBATE 80; TALC; FD&C YELLOW NO. 6 ALUMINUM LAKE; FERRIC OXIDE YELLOW; DIMETHICONE; SODIUM LAURYL SULFATE; MICROCRYSTALLINE CELLULOSE; METHACRYLIC ACID AND ETHYL ACRYLATE COPOLYMER; TRIETHYL CITRATE

482R_Albertson_21130-428_Aspirin Delayed -Release Tablets USP, 81mg EC

Active ingredient (in each tablet)

Aspirin 81 mg (NSAID)*

*nonsteroidal anti-inflammatory drug

Purpose

Pain reliever

Uses

• temporarily relieves minor aches and pain

• ask your doctor about other uses for enteric coated 81 mg Aspirin.

Warnings

Reye’s syndrome: Children and teenagers who have or are recovering from chicken pox or flu-like symptoms should not use this product. When using this product, if changes in behavior with nausea and vomiting occur, consult a doctor because these symptoms could be an early sign of Reye’s syndrome, a rare but serious illness.

Allergy alert: Aspirin may cause a severe allergic reaction which may include:•hives • facial swelling • asthma (wheezing) • shock

Stomach bleeding warning: This product contains an NSAID, which may cause severe stomach bleeding. The chance is higher if you

- are age 60 or older
- have had stomach ulcers or bleeding problem
- take a blood thinning (anticoagulant) or steroid drug
- take other drugs containing prescription or nonprescription NSAIDs (aspirin, ibuprofen, naproxen, or others)
- have 3 or more alcoholic drinks every day while using this product
- take more or for a longer time than directed

Do not use if you are allergic to aspirin or any other pain reliever/fever reducer

Ask a doctor before use if

- stomach bleeding warning applies to you
- you have a history of stomach problems, such as heartburn
- you have high blood pressure, heart disease, liver cirrhosis, or kidney disease
- you are taking a diuretic
- you have asthma

Ask a doctor or pharmacist before use if you are taking a prescription drug for gout, diabetes or arthritis

Stop use and ask a doctor if

- an allergic reaction occurs. Seek medical help right away.
- you experience any of the following signs of stomach bleeding:
- ●feel faint ● vomit blood ● have bloody or black stools ● have stomach pain that does not get better
- pain gets worse or lasts more than 10 days
- ringing in the ears or a loss of hearing occurs
- redness or swelling is present
- new symptoms occur

These could be signs of a serious condition.

PREGNANCY

If pregnant or breast-feeding, ask a health professional before use. It is especially important not to use aspirin during the last 3 months of pregnancy unless definitely directed to do so by a doctor because it may cause problems in the unborn child or complications during delivery.

Keep out of reach of children. In case of overdose, get medical help or contact a Poison Control Center (1-800-222-1222) right away.

Directions

- drink a full glass of water with each dose
- adults and children 12 years of age and over: take 4 to 8 tablets every 4 hours not to exceed 48 tablets in 24 hours unless directed by a doctor
- children under 12 years of age: do not use unless directed by a doctor

Other information

- store at 20-25°C (68-77°F)
- close cap tightly after use

INACTIVE INGREDIENT

Inactive ingredients anhydrous lactose, carnauba wax, colloidal silicon dioxide, croscarmellose sodium, FD&C red #40 aluminum lake, FD&C yellow #6 aluminum lake, iron oxide yellow, methacrylic acid and ethyl acrylate copolymer, microcrystalline cellulose, polysorbate 80, simethicone, sodium hydroxide, sodium lauryl sulfate, starch, talc, triethyl citrate

Questions or comments?1-877-290-4008